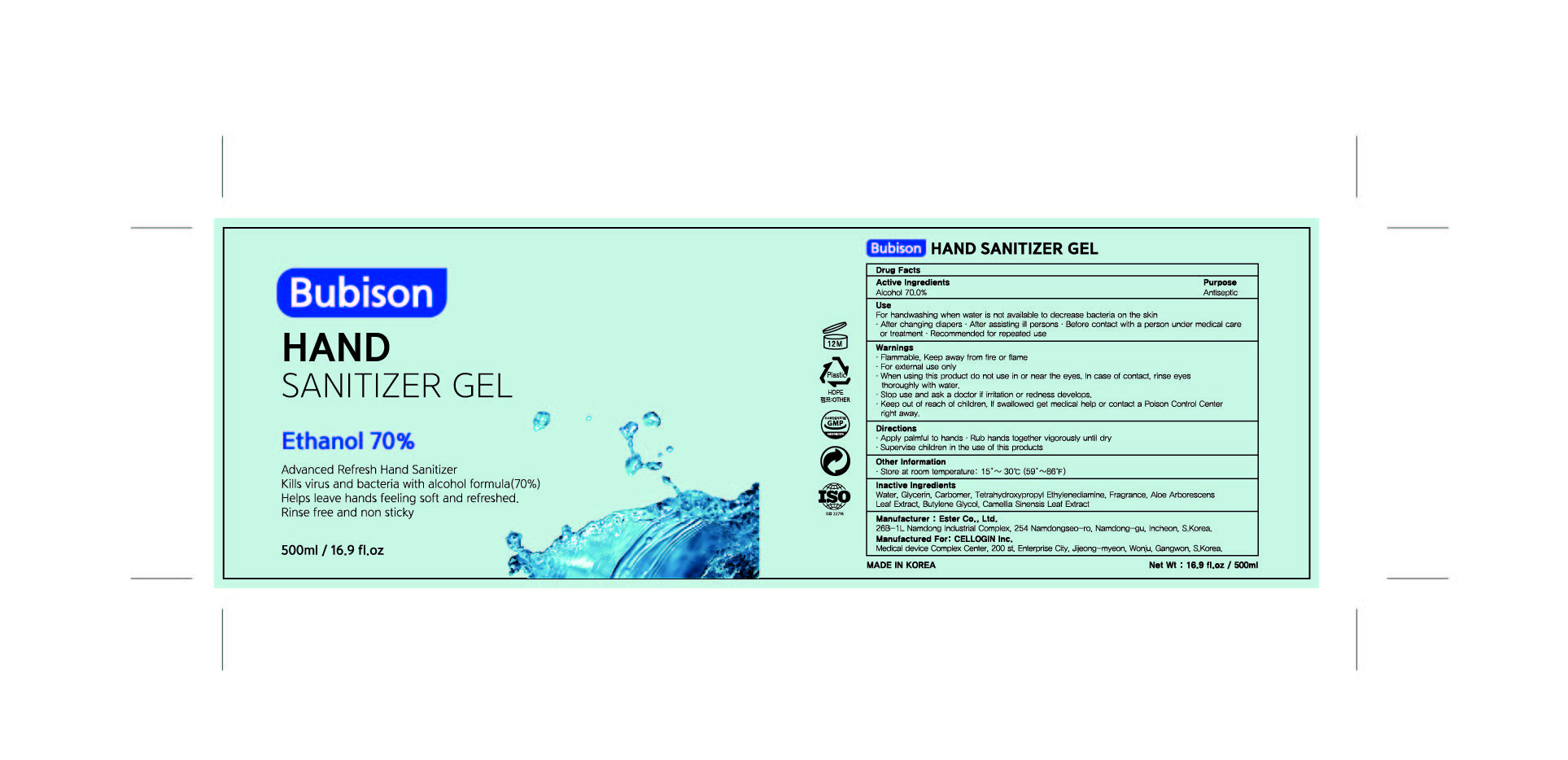 DRUG LABEL: BUBISON HAND SANITIZER Gel
NDC: 74004-570 | Form: GEL
Manufacturer: Ester Co., Ltd.
Category: otc | Type: HUMAN OTC DRUG LABEL
Date: 20200417

ACTIVE INGREDIENTS: ALCOHOL 350 g/500 mL
INACTIVE INGREDIENTS: GREEN TEA LEAF; BUTYLENE GLYCOL; EDETOL; CARBOMER HOMOPOLYMER, UNSPECIFIED TYPE; WATER; ALOE ARBORESCENS LEAF; GLYCERIN

[Ester Co., Ltd.-BUBISON HAND SANITIZER Gel] 500 ml : 74004-570-01